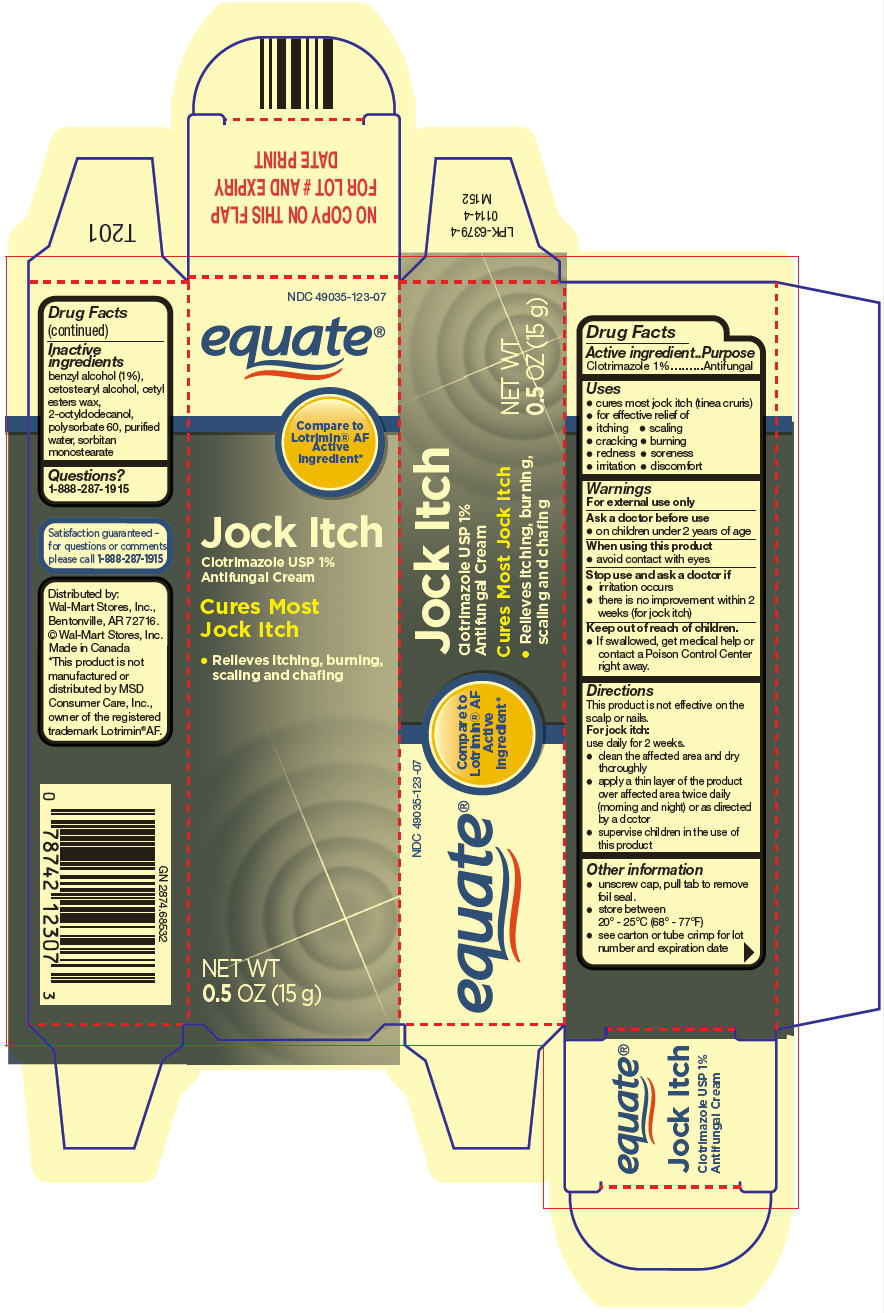 DRUG LABEL: Clotrimazole 
NDC: 49035-123 | Form: CREAM
Manufacturer: Wal-Mart Stores, Inc.
Category: otc | Type: HUMAN OTC DRUG LABEL
Date: 20140304

ACTIVE INGREDIENTS: Clotrimazole 10 mg/1 g
INACTIVE INGREDIENTS: benzyl alcohol; cetostearyl alcohol; cetyl esters wax; octyldodecanol; polysorbate 60; water; sorbitan monostearate

Clotrimazole Cream USP, 1%
Jock Itch

Drug Facts

Active ingredient

Clotrimazole 1%

Purpose

Antifungal

Uses

- cures most jock itch (tinea cruris)
- for effective relief of
  - itching
  - scaling
  - cracking
  - burning
  - redness
  - soreness
  - irritation
  - discomfort

Warnings

For external use only

Ask a doctor before use

- on children under 2 years of age

When using this product

- avoid contact with eyes

Stop use and ask a doctor if

- irritation occurs
- there is no improvement within 2 weeks (for jock itch)

Keep out of reach of children.

- If swallowed, get medical help or contact a Poison Control Center right away.

Directions

This product is not effective on the scalp or nails.

For jock itch

use daily for 2 weeks.

- clean the affected area and dry thoroughly
- apply a thin layer of the product over affected area twice daily (morning and night) or as directed by a doctor
- supervise children in the use of this product

Other information

- unscrew cap, pull tab to remove foil seal.
- store between 20° - 25°C (68° - 77°F)
- see carton or tube crimp for lot number and expiration date

Inactive ingredients

benzyl alcohol (1%), cetostearyl alcohol, cetyl esters wax, 2-octyldodecanol, polysorbate 60, purified water, sorbitan monostearate

Questions?

1-888-287-1915

Distributed by:
Wal-Mart Stores, Inc.,
Bentonville, AR 72716.

PRINCIPAL DISPLAY PANEL - 15 g Tube Carton

NDC 49035-123-07

equate®

Compare to
Lotrimin® AF
Active
Ingredient*

Jock Itch
Clotrimazole USP 1%
Antifungal Cream

Cures Most
Jock Itch

- Relieves itching, burning,
  scaling and chafing

NET WT
0.5 OZ (15 g)